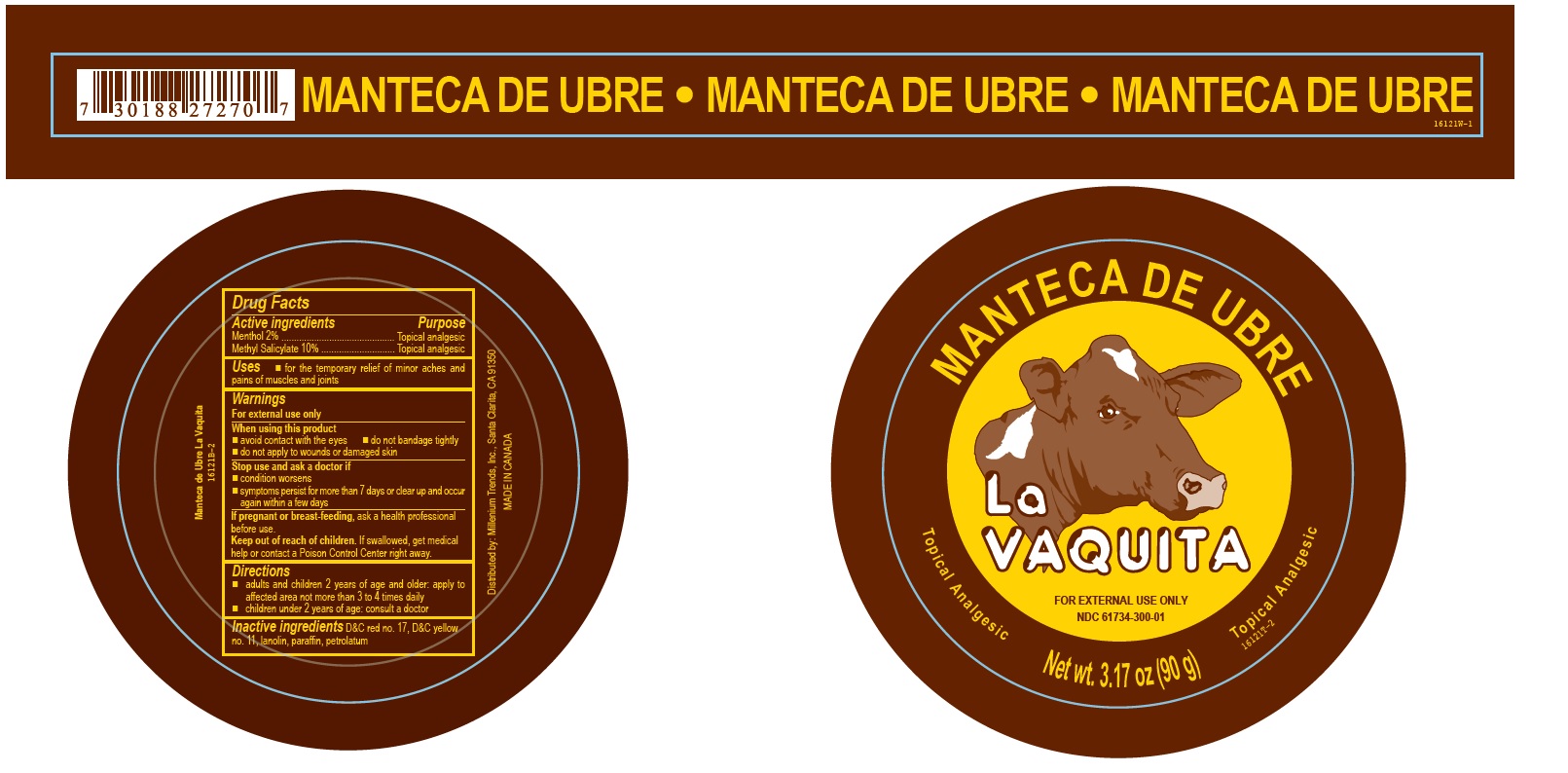 DRUG LABEL: La Vaquita New Regular
NDC: 61734-300 | Form: OINTMENT
Manufacturer: Delon Laboratories (1990) Ltd
Category: otc | Type: HUMAN OTC DRUG LABEL
Date: 20251016

ACTIVE INGREDIENTS: MENTHOL 2 g/100 g; METHYL SALICYLATE 10 g/100 g
INACTIVE INGREDIENTS: PETROLATUM; PARAFFIN; LANOLIN; D&C RED NO. 17; D&C YELLOW NO. 11

La Vaquita Regular

Active ingredients

Menthol 2%

Methyl Salicylate 10%

Purpose

Topical analgesic

Uses

- for the temporary relief of minor aches and pains of muscles and joints

Warnings

For external use only

When using this product

- avoid contact with the eyes
- do not bandage tightly
- do not apply to wounds or damaged skin

Stop use and ask a doctor if

- condition worsens
- symptoms persist for more than 7 days or clear up and occur again within a few days

PREGNANCY OR BREAST FEEDING

If pregnant or breast-feeding, ask a health professional before use.

Keep out of reach of children. If swallowed, get medical help or contact a Poison Control Center right away.

Directions

- adults and children 2 years of age and older: apply to affected area not more than 3 to 4 times daily
- children under 2 years of age: consult a doctor

Inactive ingredients

D&C red no. 17, D&C yellow no. 11, lanolin, paraffin, petrolatum